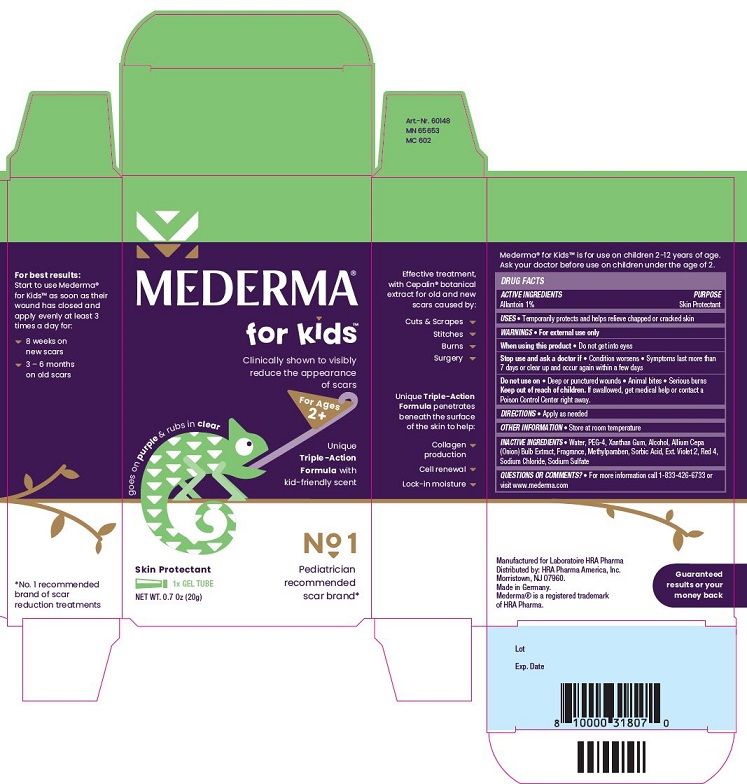 DRUG LABEL: Mederma for Kids
NDC: 73302-202 | Form: GEL
Manufacturer: HRA PHARMA AMERICA, INC.
Category: otc | Type: HUMAN OTC DRUG LABEL
Date: 20250127

ACTIVE INGREDIENTS: Allantoin 1 g/100 g
INACTIVE INGREDIENTS: Water; Polyethylene Glycol 200; Xanthan Gum; Alcohol; Onion; Methylparaben; Sorbic Acid; Ext. D&C Violet No. 2; Fd&C Red No. 4; Sodium Chloride; Sodium Sulfate

Mederma for kids DRUG FACTS

Active Ingredients

Allantoin 1%

Purpose

Skin Protectant

Uses

- Temporarily protects and helps relieve chapped or cracked skin

Warnings

- For external use only

When using this product

- Do not get into eyes

Stop use and ask a doctor if

- Condition worsens
- Symptoms last more than 7 days or clear up and occur again within a few days

Do not use on

- Deep or punctured wounds
- Animal bites
- Serious burns

Keep out of reach of children

If swallowed, get medical help or contact a Poison Control Center right away.

Directions

- Apply as needed

Other Information

- Store at room temperature

Inactive Ingredients

- Water, PEG-4, Xanthan Gum, Alcohol, Allium Cepa (Onion) Bulb Extract, Fragrance, Methylparaben, Sorbic Acid, Ext. Violet 2, Red 4, Sodium Chloride, Sodium Sulfate

Questions or Comments?

- For more information call 1-833-426-6733 or visit www.mederma.com

PRINCIPAL DISPLAY PANEL

MEDERMA® for Kids™
Clinically shown to visibly reduce the appearance of scars
For Ages 2+

goes on purple & rubs in clear
Unique Triple-Action Formula with kid-friendly scent
No 1 Pediatrician recommended scar brand
Skin Protectant
1 x GEL TUBE
NET WT. 0.7 0z (20g)